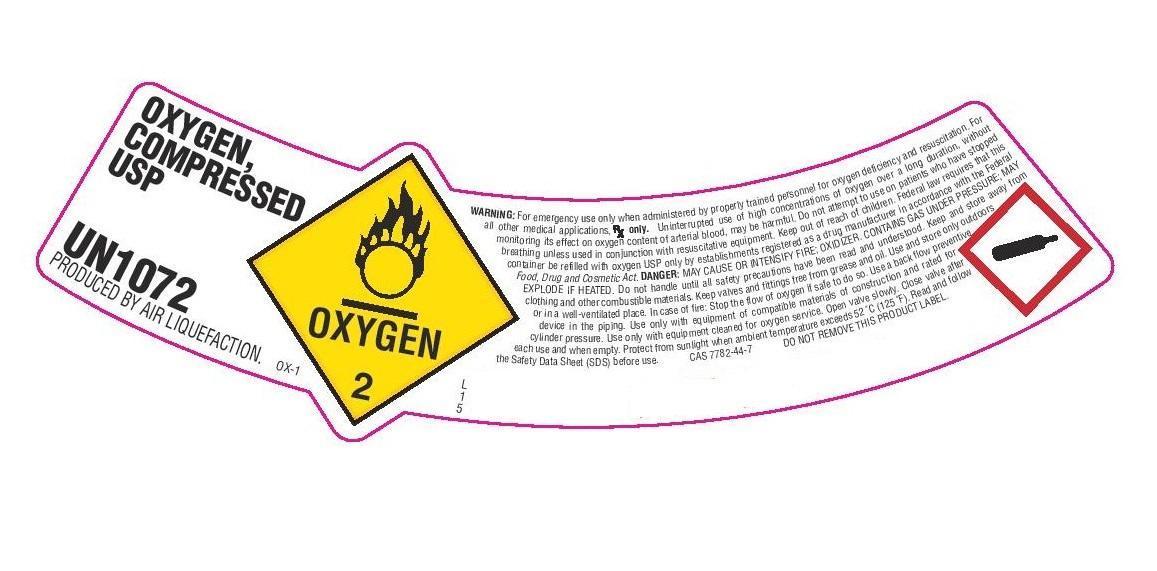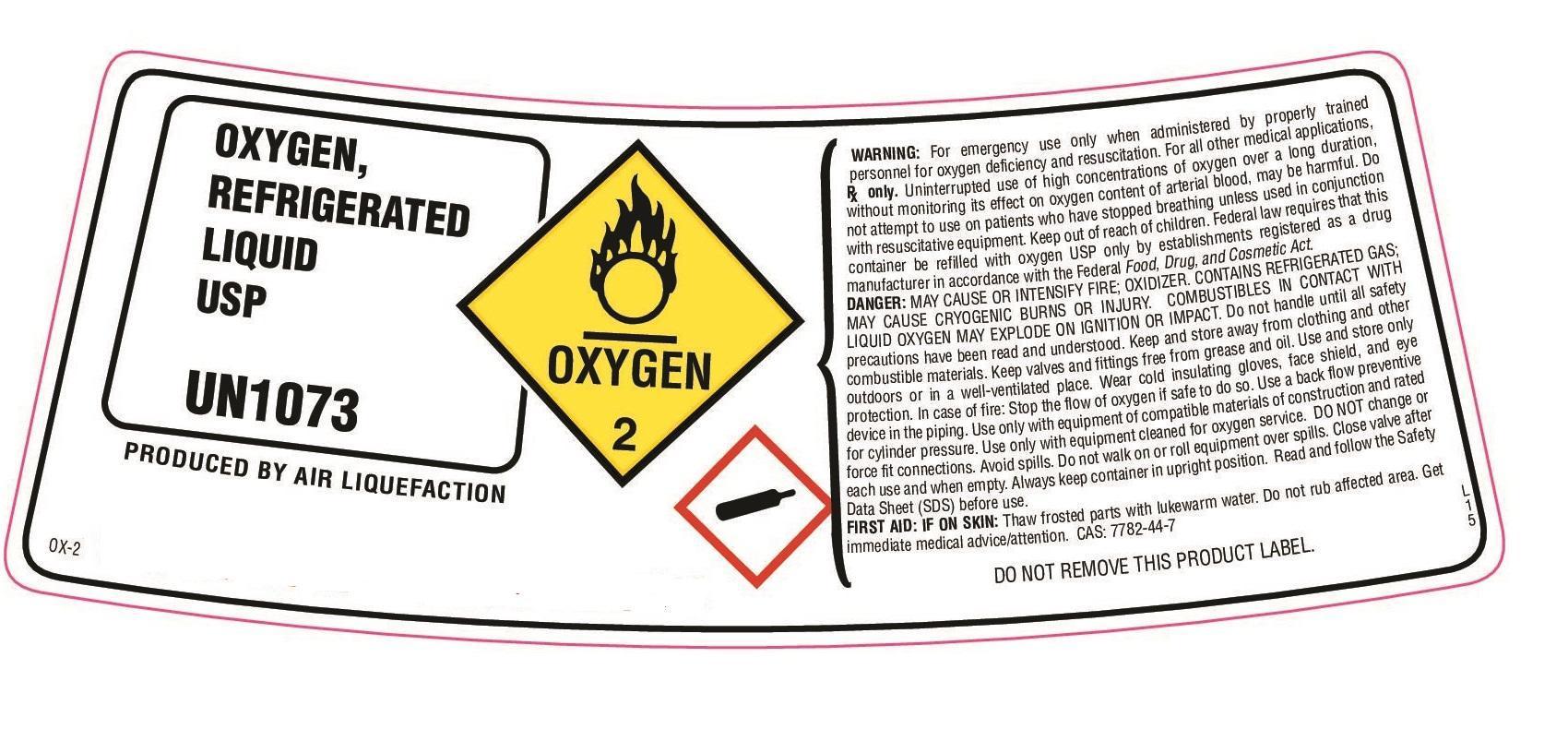 DRUG LABEL: Oxygen
NDC: 57439-000 | Form: GAS
Manufacturer: Rotech Healthcare Inc
Category: prescription | Type: HUMAN PRESCRIPTION DRUG LABEL
Date: 20180110

ACTIVE INGREDIENTS: OXYGEN 99 L/100 L

2018 DRUG REGISTRATION LISTING